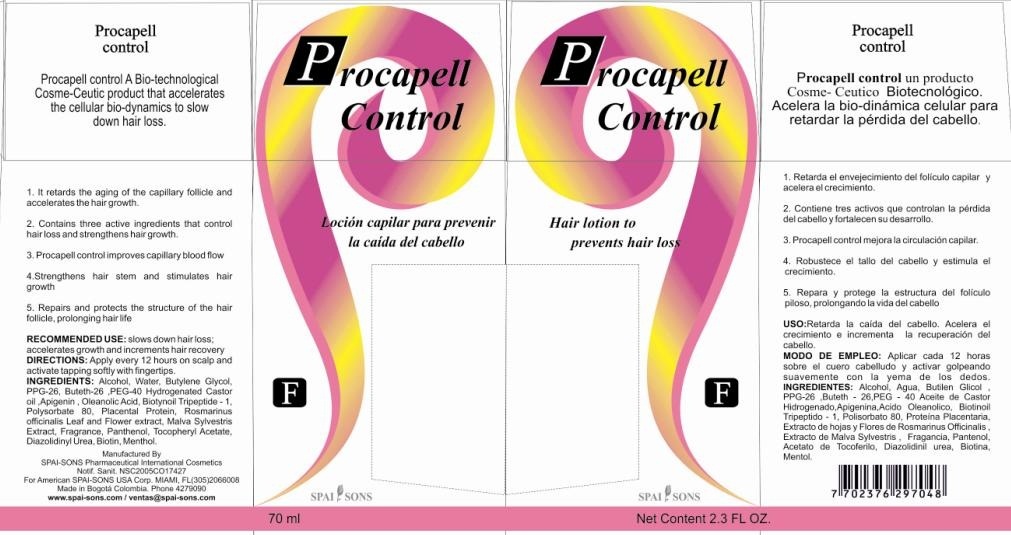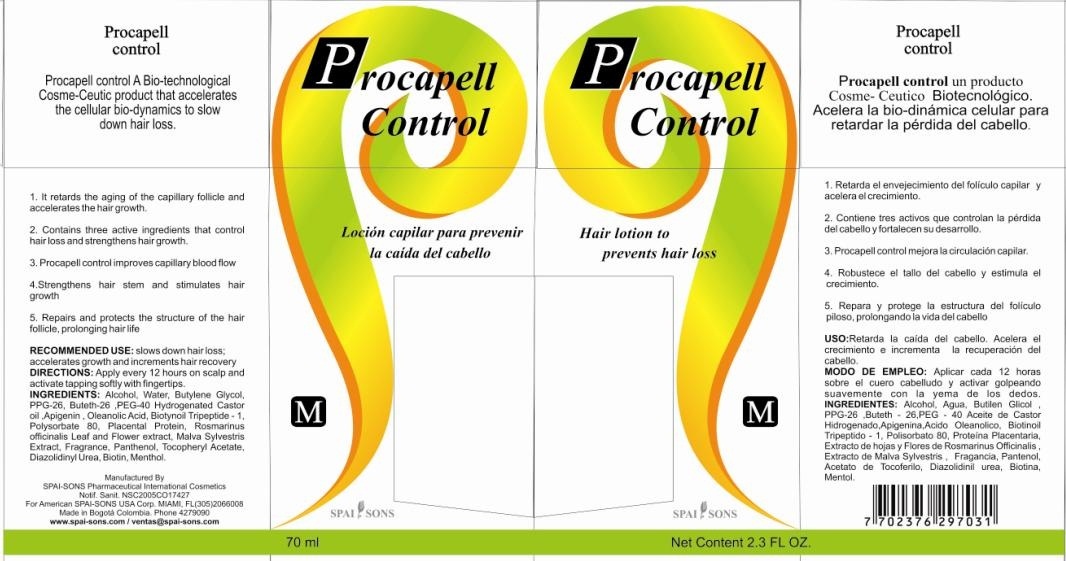 DRUG LABEL: SPAI-SONS
NDC: 66854-011 | Form: LIQUID
Manufacturer: SPAI-SONS PHARMACEUTICAL INTERNATIONAL COSMETICS
Category: otc | Type: HUMAN OTC DRUG LABEL
Date: 20120607

ACTIVE INGREDIENTS: BIOTIN 0.01 mL/100 mL
INACTIVE INGREDIENTS: ALCOHOL; WATER; BUTYLENE GLYCOL; PPG-26-BUTETH-26; POLYOXYL 40 HYDROGENATED CASTOR OIL; APIGENIN; OLEANOLIC ACID; BIOTINOYL TRIPEPTIDE-1; POLYSORBATE 80; HYDROLYZED PLACENTAL PROTEIN (BOVINE); ROSMARINUS OFFICINALIS FLOWERING TOP; MALVA SYLVESTRIS FLOWERING TOP; PANTHENOL; .ALPHA.-TOCOPHEROL ACETATE, D-; DIAZOLIDINYL UREA; MENTHOL

SPAI-SONS PROCAPELL

ACTIVE INGREDIENT

Biotin is a major component of the formulation acts to strengthen the hair follicle and prevents hair loss as well. It is nutrient for the hair root and helps oxygenate the hair turn slowing the loss. Provides resilience and resistance to hair. Addition of biotin are other ingredient such as apigenin, biotinoyl tripeptide-1 and ginkgo extract which help strengthen the hair follicle and produce a synergistic action on it.

PURPOSE

A biotechnological product that accelerates the cellular biodynamics to slow down hair loss.

1. Delays the aging process of the capillary follicle and accelerates its growth

2. Strengthens hair stem and stimulates hair growth

3. Repairs and protects the structure of the hair follicle, prolonging hair life.

KEEP OUT OF REACH OF CHILDREN

This product must be keep out reach of children

INDICATIONS AND USAGE

This product is for topical application directly on the hair follicle

WARNINGS

Avoid contact with eyes, if they do wash with water. If swallowed contact a physician immediately

DOSAGE AND ADMINISTRATION

Recommended use: slow down hair loss; accelerates growth and increments hair recovery.

Directions: apply every 12 hours on scalp and acitivate tapping softly with fingertips.

INACTIVE INGREDIENT

This is a liquid product prepared with the technology needed to provide the hair follicle absorption of the active ingredients, plus inactive ingredients contribute to the regeneration of the hair fiber by providing a strengthening therefore. No adverse effects were seen with the use of this product as inactive ingredients do not cause skin hypersensivity

IMAGE OF THE CARTON LABEL